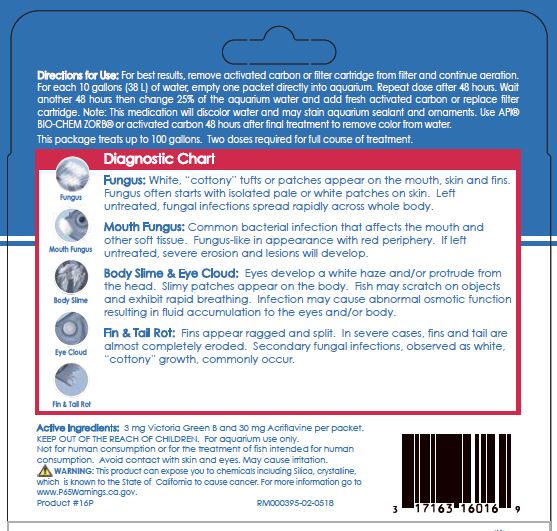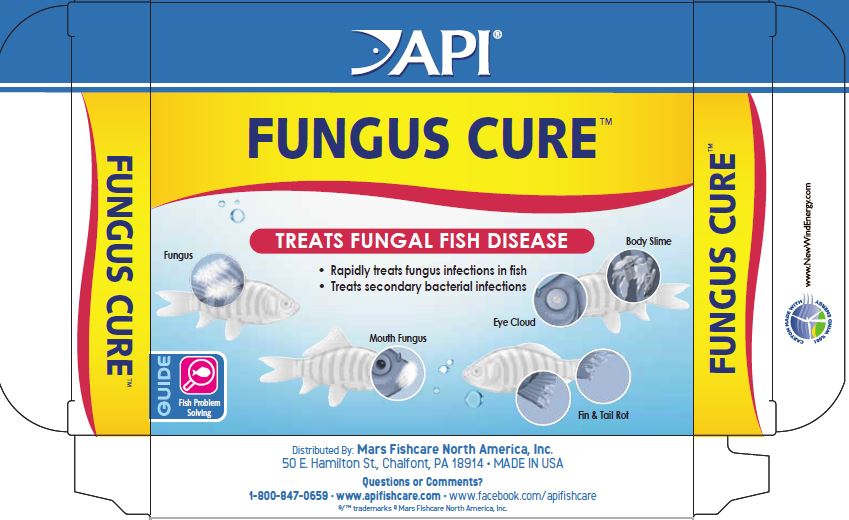 DRUG LABEL: API Fungus Cure
NDC: 17163-116 | Form: POWDER
Manufacturer: MARS FISHCARE NORTH AMERICA, INC.
Category: animal | Type: OTC ANIMAL DRUG LABEL
Date: 20201218

ACTIVE INGREDIENTS: ACRIFLAVINE HYDROCHLORIDE 30 mg/2 g; MALACHITE GREEN OXALATE 3 mg/2 g
INACTIVE INGREDIENTS: SODIUM CHLORIDE; SILICON DIOXIDE

Drug Label

ACTIVE INGREDIENT

Active Ingredients: 3 mg Victoria Green B and 30 mg Acriflavine per packet.

DOSAGE AND ADMINISTRATION

Direction for Use:

For best results, remove activated carbon or filter cartridge from filter and continue aeration.

For each 10 gallons (38 L) of water, empty one packet directly into aquarium.

Repeat dose after 48 hours.

Wait another 48 hours then change 25% of the aquarium water and add fresh activated carbon or replace filter cartridge.

Note; This medication will discolor water and may stain aquarium sealant and ornaments.

Use API BIO-CHEM ZORB or activated carbon 48 hours after final treatment to remove color from water.

This package treats up to 100 gallons. Two doses required for full course of treatment

INDICATIONS AND USAGE

Diagnostic Chart

Fungus: White, "cottony" tufts or patches appear on the mouth, skin and fins. Fungus often starts with isolated pale or white patches on skin. Left untreated, fungal infections spread rapidly across whole body.

Mouth Fungus: Common bacterial infection that affects the mouth and other soft tissue. Fungus-like in appearance with red periphery. If left untreated, severe erosion and lesions will develop.

Body Slime and Eye Cloud: Eyes develop a white haze and or protrude from the head. Slimy patches appear on the body. Fish may scratch on objects and exhibit rapid breathing.Infection may cause abnormal osmotic function resulting in fluid accumulation to the eyes and/or body.

Fin and Tail Rot: Fins appear ragged and split. In severe cases, fins and tail are almost completely eroded. Secondary fungal infections, observed as white, "cottony" growth, commonly occur.

KEEP OUT OF REACH OF CHILDREN.

For aquarium use only.

Not for human consumption or for treatment of fish intended for human consumption.

Avoid contact with skin and eyes.

May cause irritation.

! WARNING:

This product can expose you to chemicals including Silica, crystalline, which is none to the State of California to cause cancer.

For more information go to www.P65Warnings.ca.gov.

PACKAGE LABEL

Diagnostic Chart

On Back

10 Powder

Packets

Use In Freshwater Aquariums

API

FUNGUS CURE

TREATS FUNGAL FISH DISEASE

Rapidly treats fungus infections in fish

Treats secondary bacterial infections

Fungus

Body Slime

Mouth Fungus

Eye Cloud

Fin and Tail Rot

Guide

Fish Problem

Solving